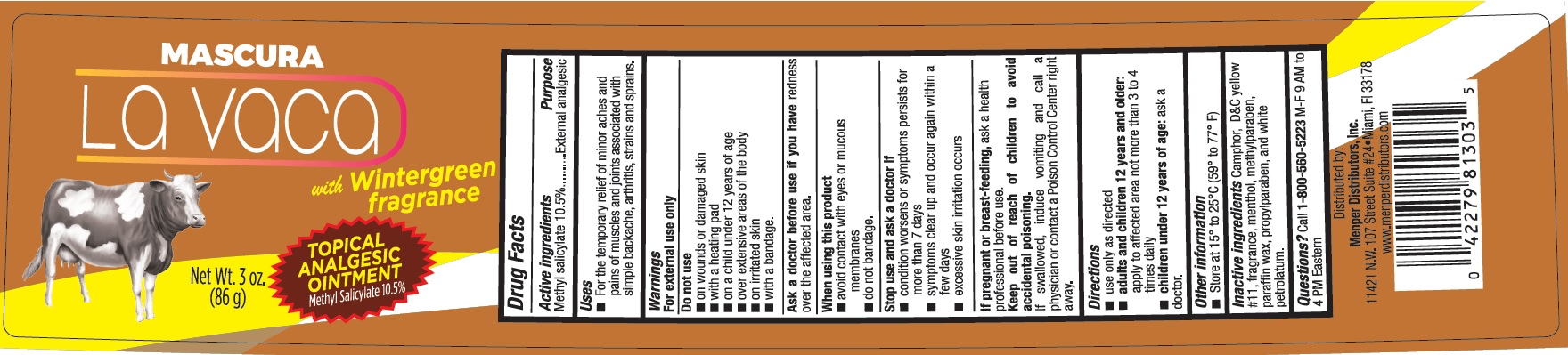 DRUG LABEL: Mascura la Vaca Plus
NDC: 53145-081 | Form: OINTMENT
Manufacturer: MENPER DISTRIBUTORS, INC.
Category: otc | Type: HUMAN OTC DRUG LABEL
Date: 20210414

ACTIVE INGREDIENTS: METHYL SALICYLATE 10.5 g/100 g
INACTIVE INGREDIENTS: CAMPHOR (SYNTHETIC); D&C YELLOW NO. 11; MENTHOL; METHYLPARABEN; PARAFFIN; PROPYLPARABEN; WHITE PETROLATUM

Active ingredients Purpose

Methyl Salicylate 10.5%...............External analgesic

Purpose

External analgesic

Uses

- For temporary relief of minor aches and pains of muscle and joints associated with simple backache, arthritis, strains and sprains.

Warnings

For external use only

Do not use

- on wounds or damaged skin
- with a heating pad
- on a child under 12 years of age
- over extensive areas of the body
- on irritated skin
- with a bandage

Ask a doctor before use if you have redness over the affected area.

When using this product

- avoid contact with eyes or mucous membranes
- do not bandage

Stop use and ask a doctor if

- condition worsens or symptoms persists for more than 7 days
- symptoms clear up and occur again within a few days
- excessive skin irritation occurs

PREGNANCY OR BREAST FEEDING

If pregnant or breast-feeding, ask a health professional before use.

Keep out of reach of children to avoid accidental poisoning. If swallowed, induce vomiting and call a physician or contact a Posion Control Center right away.

Directions

- use only as directed
- adults and children 12 years and older: apply to affected area not more than 3 to 4 times daily
- children under 12 years of age: ask a doctor.

Other information

- store at 15 to 25 C (59 to 77 F)

Inactive ingredients

Camphor, D&c red #17, fragrance, menthol, methylparaben, paraffin wax, propylparaben, and white petrolatum.

QUESTIONS

Questions: Call 1-800-560-5223 M-F 9AM to 4PM Eastern